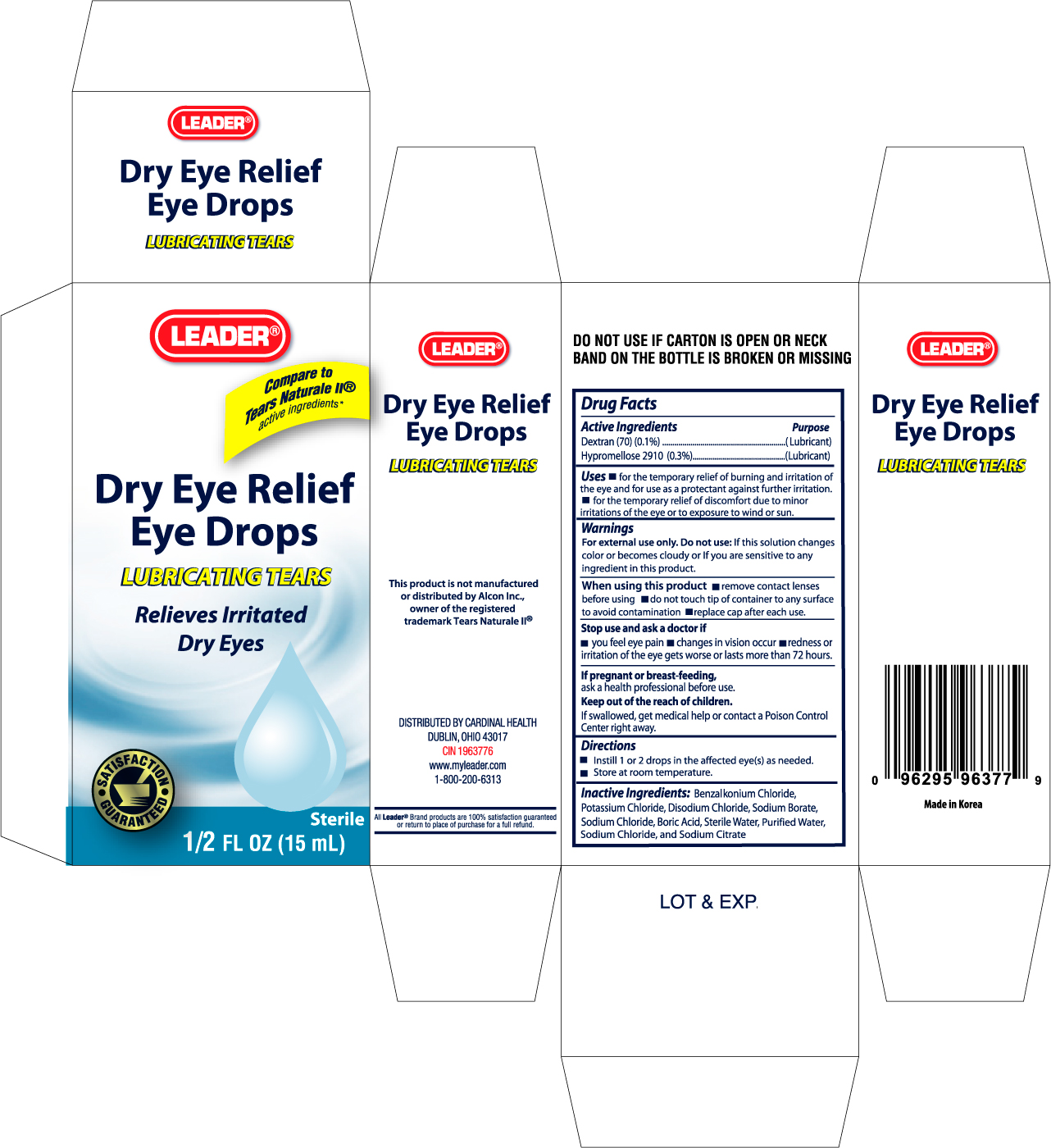 DRUG LABEL: LEADER DRY EYE RELIEF
NDC: 11716-9637 | Form: SOLUTION
Manufacturer: HANLIM PHARM. CO., LTD.
Category: otc | Type: HUMAN OTC DRUG LABEL
Date: 20100712

ACTIVE INGREDIENTS: DEXTRAN 70 0.001 mL/1 mL; HYPROMELLOSE 2910 (4000 CPS) 0.003 mL/1 mL
INACTIVE INGREDIENTS: BENZALKONIUM CHLORIDE; POTASSIUM CHLORIDE; SODIUM BORATE; SODIUM CHLORIDE; BORIC ACID; WATER; SODIUM CITRATE

Drug Facts

Active Ingredients Purpose

Dextran 70 (0.1%).........................................................................(Lubricant)

Hypromellose 2910 (0.3%).............................................................(Lubricant)

Uses

- for the temporary relief of burning and irritation of the eye and for use as a protectant against further irritation.
- for the temporary relief of discomfort due to minor irritations of the eye or to exposure to wind or sun.

Warnings

For external use only. Do not use: If this solution changes color or becomes cloudy or if you are sensitive to any ingredient in this product.

When using this product

- remove contact lenses before using
- do not touch tip of container to any surface to avoid contamination
- replace cap after each use

Stop use and ask a doctor if

- you feel pain
- changes in vision occur
- redness or irritation of the eye gets worse or lasts more than 72 hours

If pregnant or breast-feeding,

ask a health professional before use.

Keep out of the reach of children.

If swallowed, get medical help or contact a Poison Control Center right away.

Directions

- Instill 1 or 2 drops in the affected eye(s) as needed.
- Store at room temperature

INACTIVE INGREDIENT

Inactive Ingredients: Benzalkonium Chloride, Potassium Chloride, Disodium Chloride, Sodium Borate, Sodium Chloride, Boric Acid, Sterile Water, Purified Water, Sodium Chloride, and Sodium Citrate

PACKAGE LABEL

Enter section text here